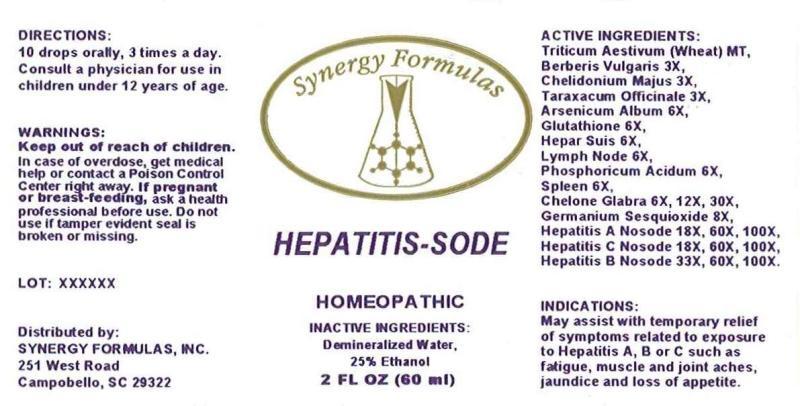 DRUG LABEL: HEPATITIS-SODE
NDC: 43772-0029 | Form: LIQUID
Manufacturer: Synergy Formulas, Inc.
Category: homeopathic | Type: HUMAN OTC DRUG LABEL
Date: 20150421

ACTIVE INGREDIENTS: TRITICUM AESTIVUM WHOLE 1 [hp_X]/1 mL; BERBERIS VULGARIS ROOT BARK 3 [hp_X]/1 mL; CHELIDONIUM MAJUS 3 [hp_X]/1 mL; TARAXACUM OFFICINALE 3 [hp_X]/1 mL; ARSENIC TRIOXIDE 6 [hp_X]/1 mL; GLUTATHIONE 6 [hp_X]/1 mL; PORK LIVER 6 [hp_X]/1 mL; SUS SCROFA LYMPH 6 [hp_X]/1 mL; PHOSPHORIC ACID 6 [hp_X]/1 mL; SUS SCROFA SPLEEN 6 [hp_X]/1 mL; CHELONE GLABRA 6 [hp_X]/1 mL; GERMANIUM SESQUIOXIDE 8 [hp_X]/1 mL; HEPATITIS A VIRUS 18 [hp_X]/1 mL; HEPATITIS C VIRUS 18 [hp_X]/1 mL; HEPATITIS B VIRUS 33 [hp_X]/1 mL
INACTIVE INGREDIENTS: WATER; ALCOHOL

DRUG FACTS:

ACTIVE INGREDIENTS:

Triticum Aestivum (Wheat) Mt, Berberis Vulgaris 3X, Chelidonium Majus 3X, Taraxacum Officinale 3X, Arsenicum Album 6X, Glutathione 6X, Hepar Suis 6X, Lymph (Suis) 6X, Phosphoricum Acidum 6X, Spleen (Suis) 6X, Chelone Glabra 6X, 12X, 30X, Germanium Sesquioxide 8X, Hepatitis A Nosode 18X, 60X, 100X, Hepatitis C Nosode 18X, 60X, 100X, Hepatitis B Nosode 33X, 60X, 100X.

INDICATIONS:

May assist with temporary relief of symptoms related to exposure to Hepatitis A, B or C such as fatigue, muscle and joint aches, jaundice and loss of appetite.

WARNINGS:

Keep out of reach of children. In case of overdose, get medical help or contact a Poison Control Center right away.

If pregnant or breast-feeding, ask a health professional before use.

Do not use if tamper evident seal is broken or missing.

Keep out of reach of children. In case of overdose, get medical help or contact a Poison Control Center right away.

DIRECTIONS:

10 drops orally, 3 times a day. Consult a physician for use in children under 12 years of age.

INDICATIONS:

May assist with temporary relief of symptoms related to exposure to Hepatitis A, B or C such as fatigue, muscle and joint aches, jaundice and loss of appetite.

INACTIVE INGREDIENTS:

Demineralized Water, 25% Ethanol

QUESTIONS:

Distributed by:

SYNERGY FORMULAS, INC.

251 West Road

Campobello, SC 29322

PACKAGE LABEL DISPLAY:

Synergy Formulas

HEPATITIS-SODE

HOMEOPATHIC

2 FL OZ (60 ml)